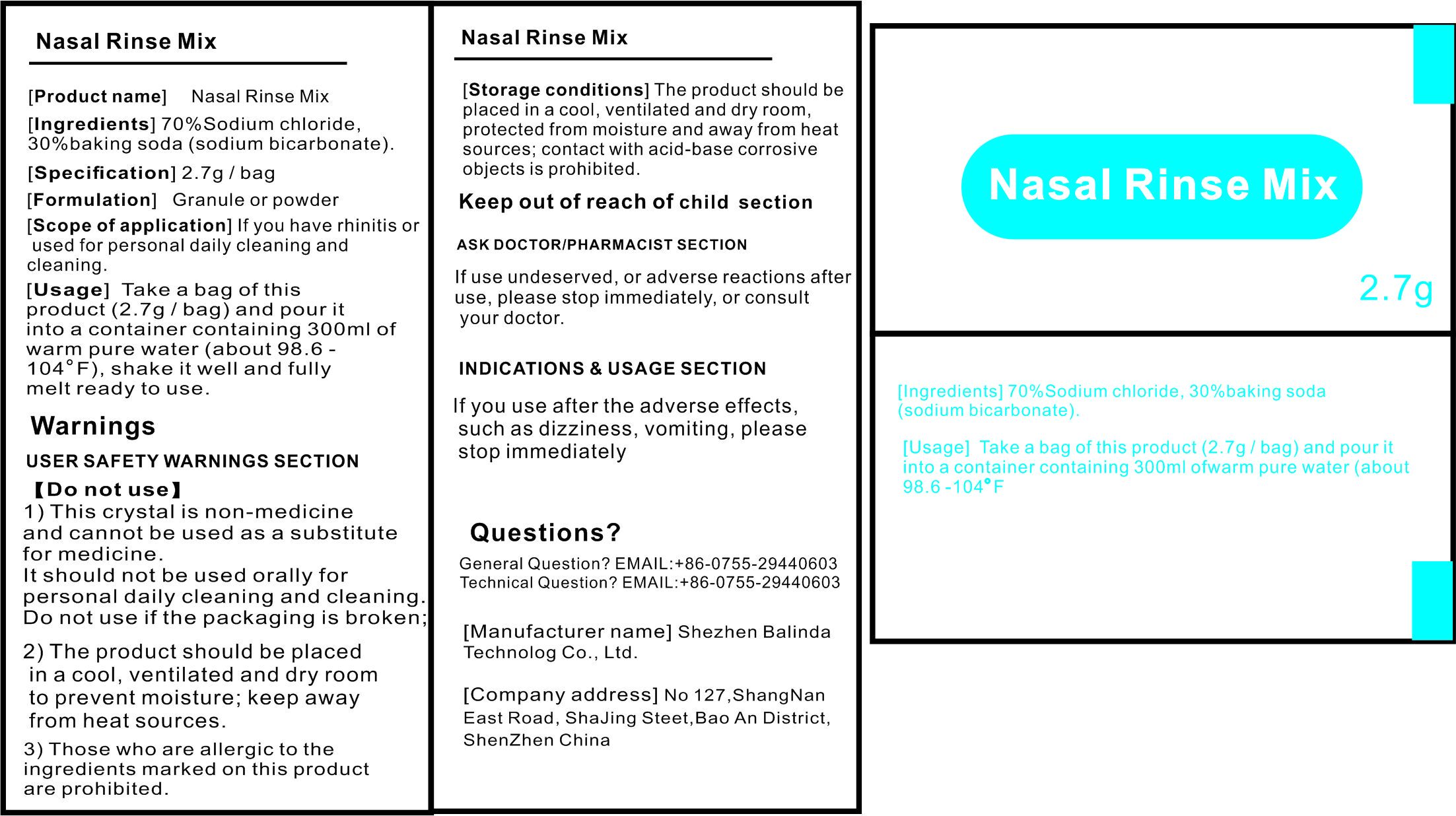 DRUG LABEL: Nasal Rinse Mix
NDC: 73843-001 | Form: LIQUID
Manufacturer: Shenzhen Balinda Technology Co.,Ltd
Category: otc | Type: HUMAN OTC DRUG LABEL
Date: 20200331

ACTIVE INGREDIENTS: ALCOHOL 1 g/100 g
INACTIVE INGREDIENTS: WATER; SODIUM CHLORIDE; SODIUM BICARBONATE

Nasal Rinse Mix

Active Ingredient

70%Sodium Chloride,30%baking soda(sodium bicarbonate).

Use

lf you use after the adverse effects,such as dizziness,vomiting, please stop immediately

Warnings

USER SAFETY WARNINGS SECTION

Do not use

1)This crystal is non-medicine and cannot be used as a substitute for medicine.

It should not be used orally for personal daily cleaning and cleaning .

Do not use if the packaging is broken；

2)The product should be placed in a cool,ventilated and dry room to prevent moisture;keep away

from heat sources.

3)Those who are allergic to the

ingredients marked on this product

are prohibited.